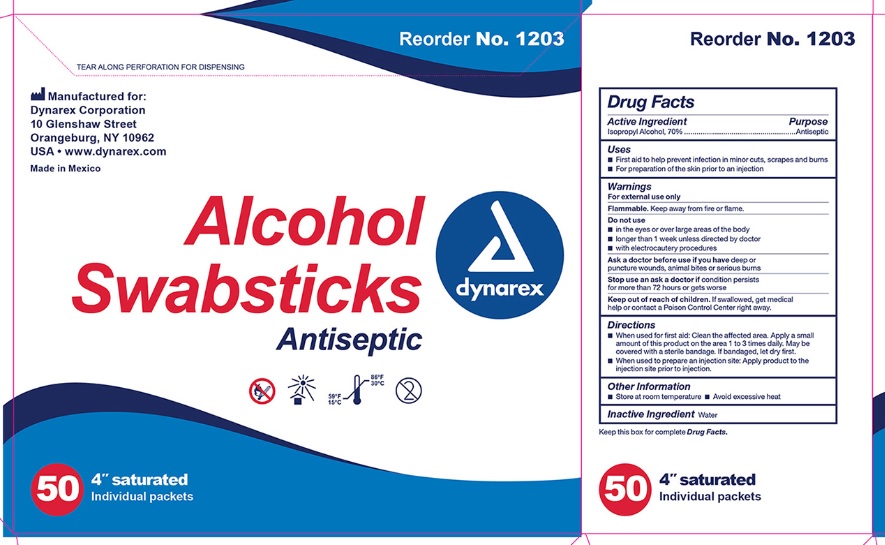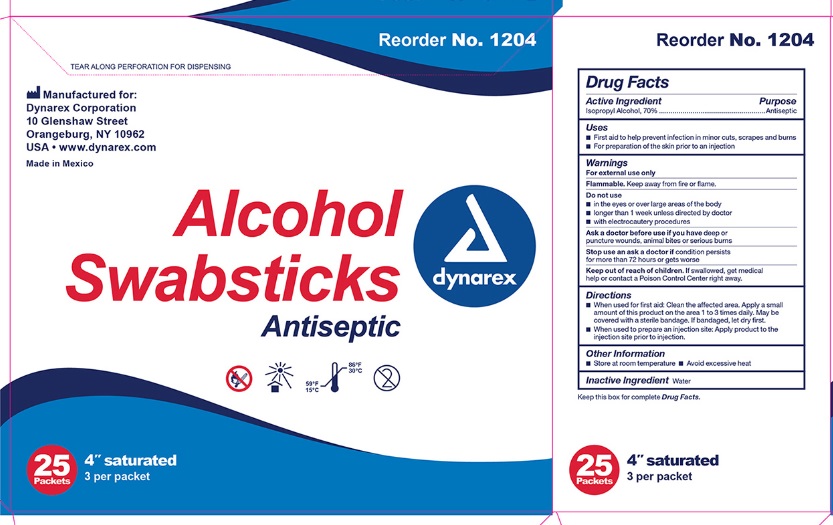 DRUG LABEL: Alcohol
NDC: 68786-300 | Form: SWAB
Manufacturer: Sion Biotext Medical Ltd
Category: otc | Type: HUMAN OTC DRUG LABEL
Date: 20240124

ACTIVE INGREDIENTS: ISOPROPYL ALCOHOL 0.7 mL/1 mL
INACTIVE INGREDIENTS: WATER

Alcohol Swabsticks

Active Ingredient

Isopropyl Alcohol 70% v/v

Purpose

Antiseptic

Uses

First aid to help prevent infection in minor cuts, scrapes and burns

For preparation of the skin prior to an injection

Warnings

- For external use only
- Flammable, keep away from flame or fire

Do not use

- in the eyes or over large areas of the body
- longer than 1 week unless directed by doctor
- with electrocautery procedures

Ask a doctor before use if you have

deep or puncture wounds, animal bites or serious burns

Stop use an ask a doctor if

conditions persists for more than 72 hours or gets worse

Keep out of reach of children.

If swallowed, get medical help or contact a Poison Control Center right away.

Directions:

- When used for first aid: Clean the affected area. Apply a small amount of this product on the area 1 to 3 times daily. May be covered with a sterile bandage. If bandaged, let dry first.
- When used to prepare an injection site: Apply product to the injection site prior to injection.

Other Information:

- Store at room temperature
- Avoid excessive heat

Inactive Ingredient

Water

Principal Display Panel

NDC 68786-300-01

4'' saturated

50 individual packs

NDC 68786-300-02

4" saturated

3 per packet

25 packet